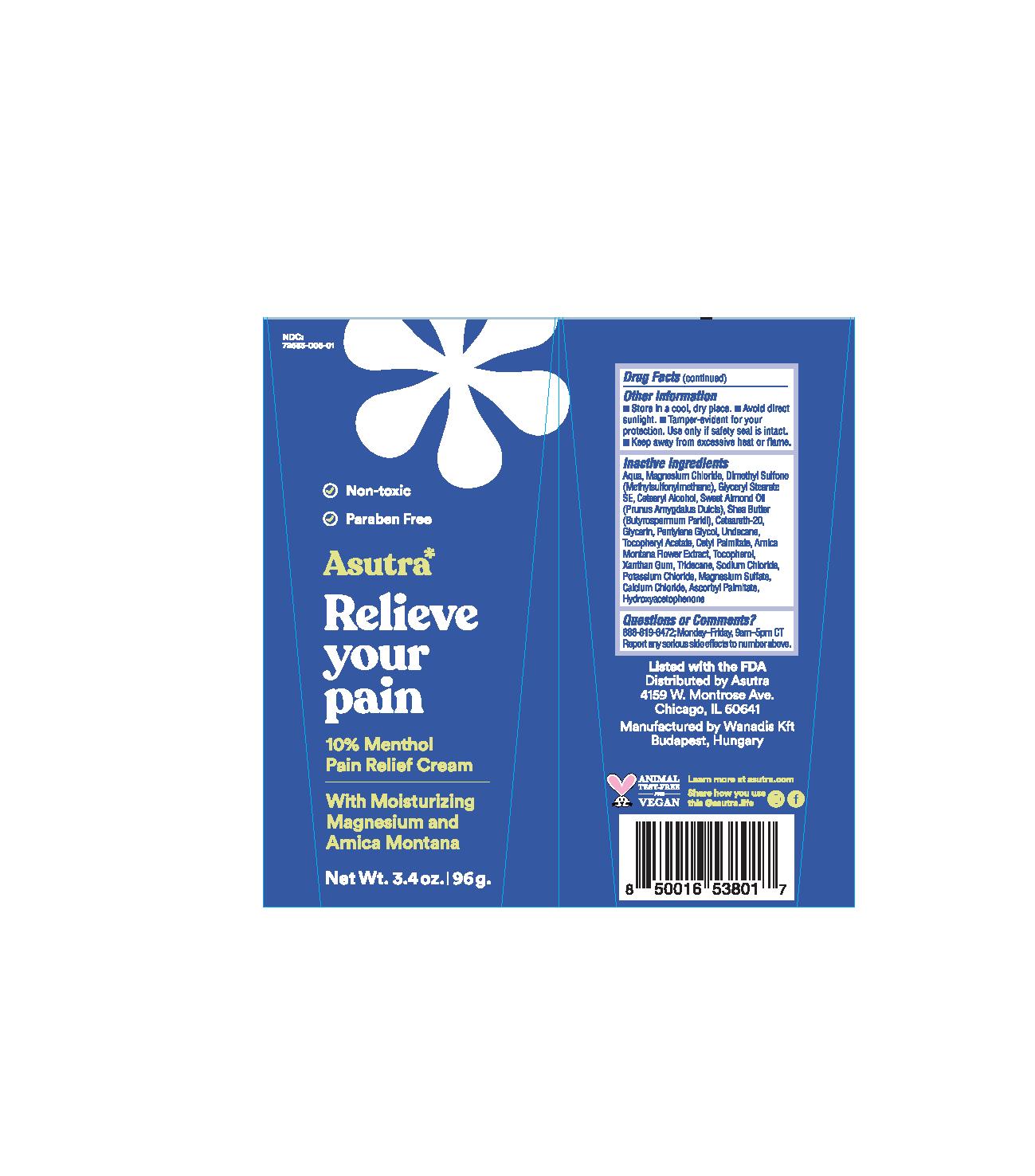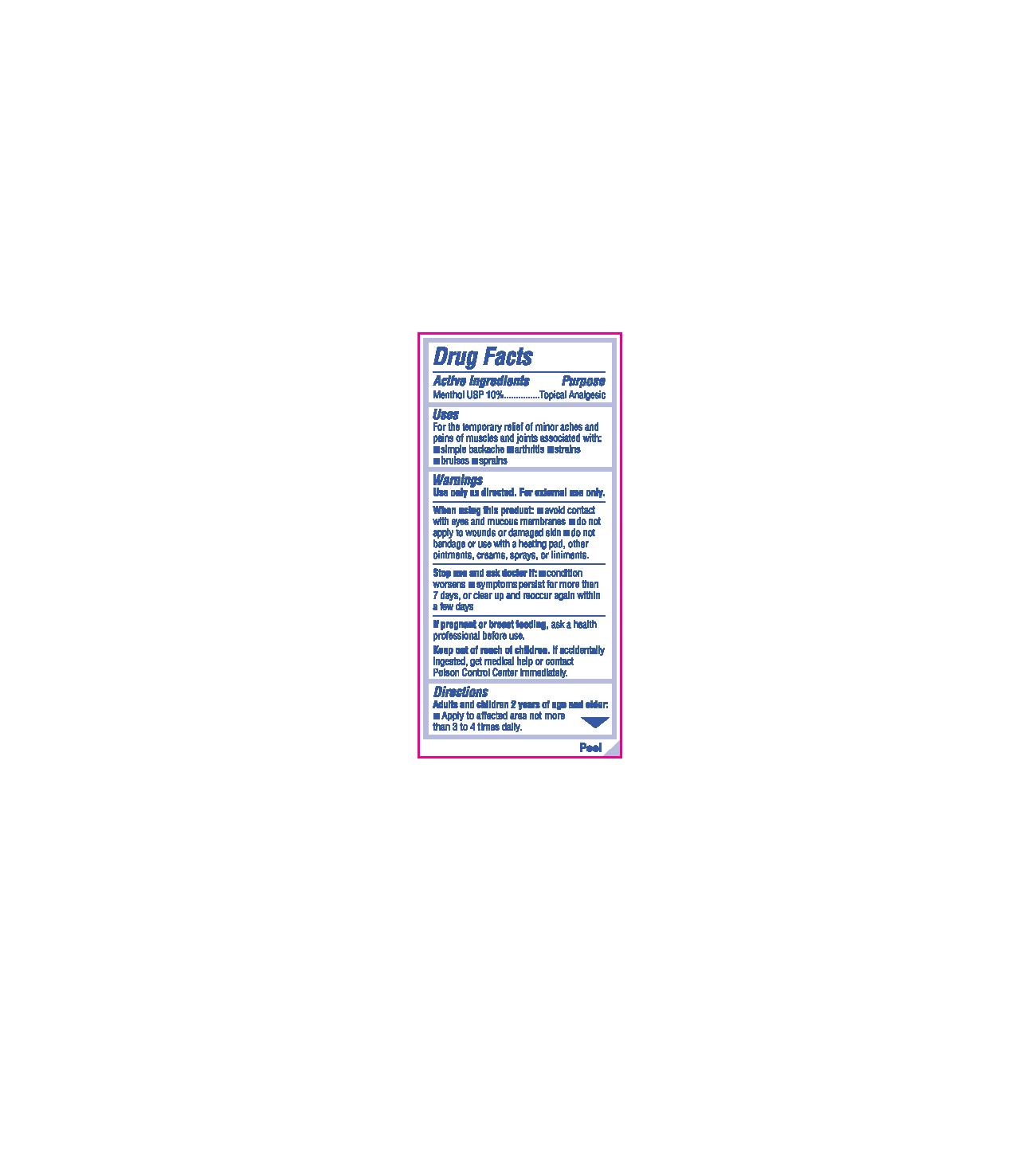 DRUG LABEL: Relieve Your Pain
NDC: 72683-005 | Form: CREAM
Manufacturer: Proximity Capital Partners LLC dba Asutra
Category: otc | Type: HUMAN OTC DRUG LABEL
Date: 20250618

ACTIVE INGREDIENTS: MENTHOL 10 g/100 g
INACTIVE INGREDIENTS: GLYCERYL STEARATE SE; ALMOND OIL; TRIDECANE; GLYCERIN; PENTYLENE GLYCOL; ALPHA-TOCOPHEROL ACETATE; CETYL PALMITATE; ARNICA MONTANA FLOWER; TOCOPHEROL; XANTHAN GUM; POTASSIUM CHLORIDE; MAGNESIUM SULFATE, UNSPECIFIED FORM; CALCIUM CHLORIDE; HYDROXYACETOPHENONE; SODIUM CHLORIDE; SHEA BUTTER; POLYOXYL 20 CETOSTEARYL ETHER; UNDECANE; ASCORBYL PALMITATE; DIMETHYL SULFONE; WATER; MAGNESIUM CHLORIDE

Relieve Your Pain (Asutra)

Active Ingredients

Menthol USP 10%

Purpose

Menthol USP 10%.....................Topical Analgesic

Uses

For the temporary relief of minor aches and pains of muscles and joints associated with:

- simple backache
- arthritis
- strains
- bruises
- sprains

Warnings

Use only as directed. For external use only.

When using this product:

- avoid contact with eyes and mucous membranes
- do not apply to wounds or damaged skin
- do not bandage or use with a heating pad, other ointments, creams, sprays, or liniments.

Stop use and ask doctor if:

- condition worsens
- symptoms persist for more than 7 days, or clear up and reoccur again within a few days

PREGNANCY OR BREAST FEEDING

If pregnant or breast feeding,ask a health professional before use.

Keep out of reach of children.If accidentally ingested, get medical help or contact Poison Control Center immediately.

Directions

Adults and children 2 years of age and older:

- Apply to affected area not more than 3 to 4 times daily.

Other Information

- Store in a cool, dry place.
- Avoid direct sunlight.
- Tamper-evident for your protection. Use only if safety seal is intact.
- Keep away from excessive heat or flame.

Inactive Ingredients

Aqua, Magnesium Chloride, Dimethyl Sulfone (Methylsulfonylmethane), Glyceryl Stearate SE, Cetearyl Alcohol, Sweet Almond Oil (Prunus Amygdalus Dulcis), Shea Butter (Butyrospermum Parkii), Ceteareth-20, Glycerin, Pentylene Glycol, Undecane, Tocopheryl Acetate, Cetyl Palmitate, Arnica Montana Flower Extract, Tocopherol, Xanthan Gum, Tridecane, Sodium Chloride, Potassium Chloride, Magnesium Sulfate, Calcium Chloride, Ascorbyl Palmitate, Hydroxyacetophenone

Questions or Comments?

888-819-6472; Monday-Friday, 9am-5pm CT

Report any serious side effects to number above.

PACKAGE LABEL

NDC 72683-005-01

Non-toxic

Paraben Free

Asutra*

Relieve

your

pain

10% Menthol

Pain Relief Cream

With Moisturizing

Magnesium and

Arnica Montana

Net Wt. 3.4 oz. | 96 g.